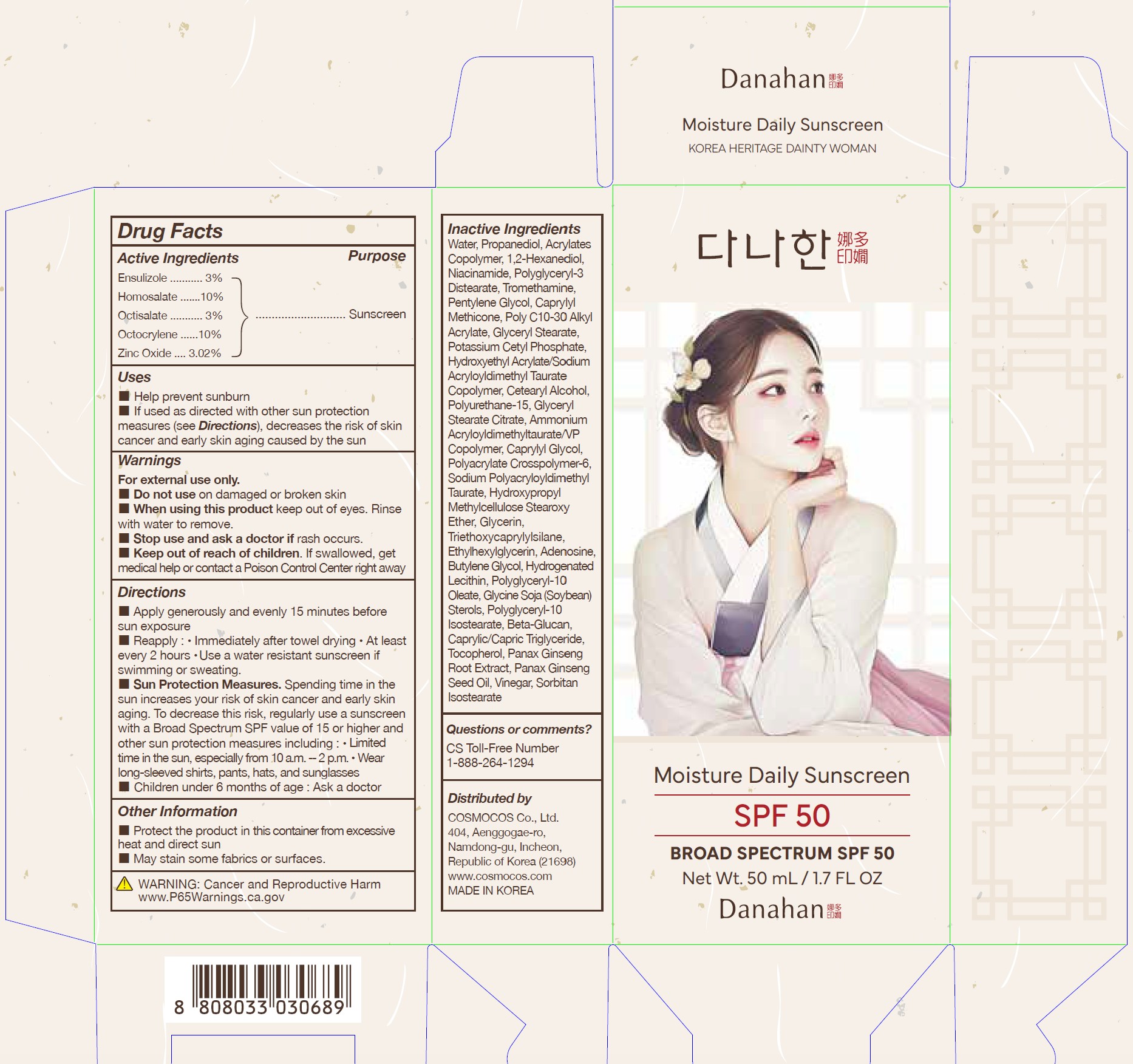 DRUG LABEL: Danahan Moisture Daily Sunscreen Broad Spectrum SPF 50
NDC: 83305-001 | Form: CREAM
Manufacturer: Cosmocos Co., Ltd
Category: otc | Type: HUMAN OTC DRUG LABEL
Date: 20251017

ACTIVE INGREDIENTS: OCTOCRYLENE 10 mg/1 mL; HOMOSALATE 10 mg/1 mL; ZINC OXIDE 3.02 mg/1 mL; OCTISALATE 3 mg/1 mL; ENSULIZOLE 3 mg/1 mL
INACTIVE INGREDIENTS: WATER

83305-001-50 Danahan Moisture Daily Sunscreen Broad Spectrum SPF 50

Drug Facts

ACTIVE INGREDIENTS

Ensulizole 3%
Homosalate 10%
Octisalate 3%
Octocrylene 10%
Zinc Oxide 3.02%

PURPOSE

Sunscreen

USES

- Helps prevent sunburn
- If used as directed with other sun protection measures (see Directions), decreases the risk of skin cancer and early skin aging caused by the sun

WARNINGS

For external use only.

- Do not use on damaged or broken skin

- When using this product keep out of the eyes. Rinse with water to remove.

- Stop use and ask a doctor if rash occurs.

- Keep out of reach of children. If swallowed, get medical help or contact a Poison Control Center right away

DIRECTIONS

- Apply generously and evenly 15 minutes before sun exposure
- Reapply:
- Immediately after towel drying
- At least every 2 hours
- Use a water resistant sunscreen if swimming or sweating
- Sun Protection Measures. Spending time in the sun increases your risk of skin cancer and early skin aging. To decrease this risk, regularly use a sunscreen with a Broad Spectrum SPF value of 15 or higher and other sun protection measures including:
- Limit time in the sun, especially from 10 a.m.-2 p.m.
- Wear long-sleeved shirts, pants, hats, and sunglasses
- Children under 6 months of age: Ask a doctor

OTHER INFORMATION

- Protect the product in this container from excessive heat and direct sun
- May stain some fabrics or surfaces.

INACTIVE INGREDIENTS

Water, Propanediol, Acrylates Copolymer, 1,2-Hexanediol, Niacinamide, Polyglyceryl-3 Distearate, Tromethamine, Pentylene Glycol, Caprylyl Methicone, Poly C10-30 Alkyl Acrylate, Glyceryl Stearate, Potassium Cetyl Phosphate, Hydroxyethyl Acrylate/Sodium Acryloyldimethyl Taurate Copolymer, Cetearyl Alcohol, Polyurethane-15, Glyceryl Stearate Citrate, Ammonium Acryloyldimethyltaurate/VP Copolymer, Caprylyl Glycol, Polyacrylate Crosspolymer-6, Sodium Polyacryloyldimethyl Taurate, Hydroxypropyl Methylcellulose Stearoxy Ether, Glycerin, Triethoxycaprylylsilane, Ethylhexylglycerin, Adenosine, Butylene Glycol, Hydrogenated Lecithin, Polyglyceryl-10 Oleate, Glycine Soja (Soybean) Sterols, Polyglyceryl-10 Isostearate, Beta-Glucan, Caprylic/Capric Triglyceride, Tocopherol, Panax Ginseng Root Extract, Panax Ginseng Seed Oil, Vinegar, Sorbitan Isostearate

QUESTIONS OR COMMENTS?

CS Toll-Free Number
1-888-264-1294
Distributed by

COSMOCOS Co., ltd.
404, Aenggogae-ro,
Namdong-gu, Incheon,
Republic of Korea (21698)
www.cosmocos.com
MADE IN KOREA

PRINCIPAL DISPLAY PANEL: 50 mL / 1.7 FL OZ Carton

Moisture Daily Sunscreen
SPF 50
BROAD SPECTRUM SPF 50
Net Wt. 50 mL / 1.7 FL OZ
Danahan